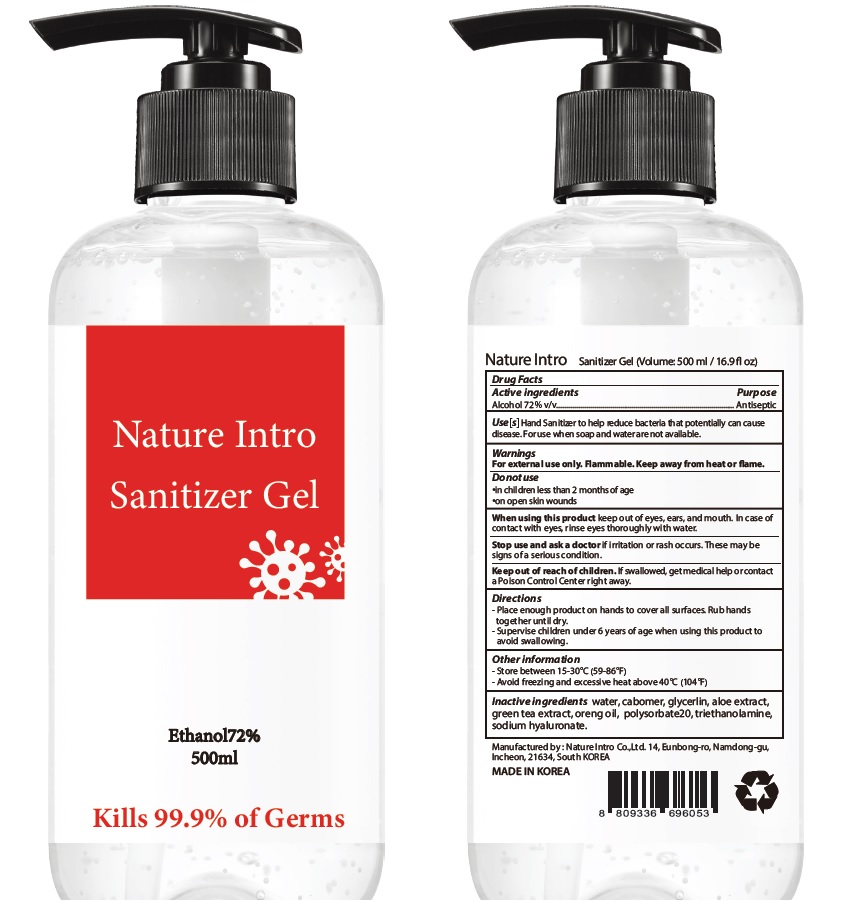 DRUG LABEL: NATURE INTRO SANITIZER
NDC: 78222-020 | Form: GEL
Manufacturer: Nature Intro Co., Ltd.
Category: otc | Type: HUMAN OTC DRUG LABEL
Date: 20200612

ACTIVE INGREDIENTS: ALCOHOL 72 mL/100 mL
INACTIVE INGREDIENTS: Water; CARBOMER HOMOPOLYMER, UNSPECIFIED TYPE; glycerin; ALOE; GREEN TEA LEAF; ORANGE OIL; polysorbate 20; TROLAMINE; HYALURONATE SODIUM

ACTIVE INGREDIENT

Ethyl alcohol 72% v/v

INACTIVE INGREDIENTS

Water, carbomer, glycerin, aloe extract, green tea extract, orange oil, polysorbate20, triethanolamine, sodium hyaluronate

PURPOSE

ANTISEPTIC

WARNINGS

For external use only. Flammable. Keep away from heat or flame
--------------------------------------------------------------------------------------------------------
Do not use
• in children less than 2 months of age
• on open skin wounds
--------------------------------------------------------------------------------------------------------
When using this product keep out of eyes, ears, and mouth. In case of contact with eyes, rinse eyes thoroughly with water.
--------------------------------------------------------------------------------------------------------
Stop use and ask a doctor if irritation or rash occurs. These may be signs of a serious condition.

KEEP OUT OF REACH OF CHILDREN

If swallowed, get medical help or contact a Poison Control Center right away.

Use(s)

Hand Sanitizer to help reduce bacteria that potentially can cause disease.

For use when soap and water are not available.

Directions

• Place enough product on hands to cover all surfaces. Rub hands together until dry.
• Supervise children under 6 years of age when using this product to avoid swallowing.

Other Information

• Store between 15-30℃ (59-86℉)
• Avoid freezing and excessive heat above 40℃ (104℉)